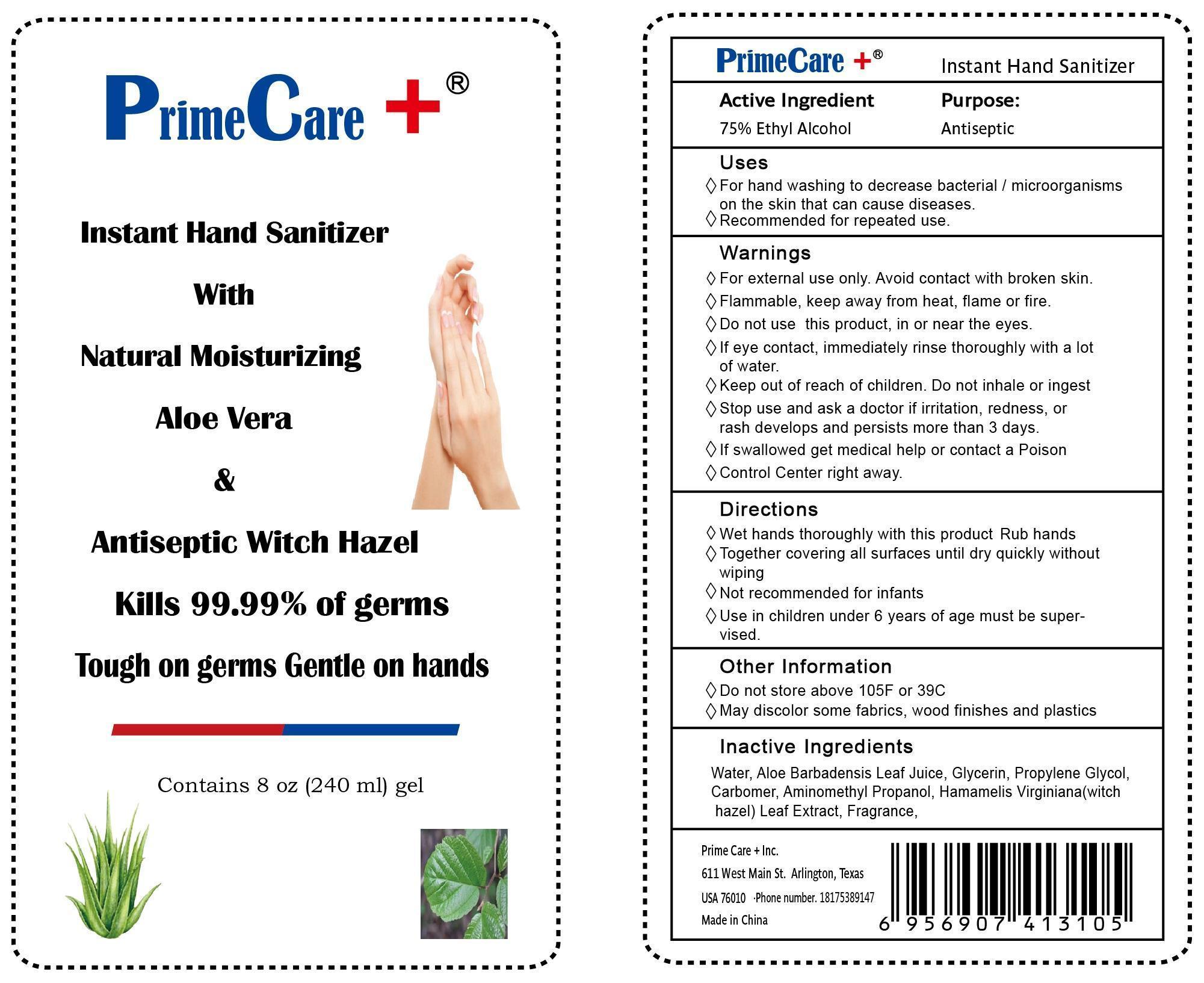 DRUG LABEL: Instant Hand Sanitizer
                
                
NDC: 69410-0001 | Form: GEL
Manufacturer: PrimeCare + Inc.
Category: otc | Type: HUMAN OTC DRUG LABEL
Date: 20141126

ACTIVE INGREDIENTS: Alcohol 75 mL/100 mL
INACTIVE INGREDIENTS: WATER; GLYCERIN; PROPYLENE GLYCOL; CARBOMER INTERPOLYMER TYPE A (ALLYL SUCROSE CROSSLINKED); AMINOMETHYLPROPANOL; ALOE VERA LEAF; HAMAMELIS VIRGINIANA LEAF WATER

Active Ingredient

75% Ethyl Alcohol

Purpose
Antiseptic

Uses:

- For hand washing to decrease bacteria/microorganisms on the skin that can cause diseases.
- Recommended for repeated use.

Warnings:

◊ For external use only. Avoid contact with broken skin.
◊ Flammable, keep away from heat, flame or fire.◊ Do not use this product,in or near the eyes.
◊ If eye contact, immediately rinse thoroughly with a lot of water.

- Stop use and ask a doctor if irritation, redness, or rash develops and persists for more than 3 days.
- If swallowed, get medical help or contact a Poison Control Center right away.

Keep out of reach of children. Do not inhale or ingest.

Directions:

◊ Wet hands thoroughly with product ◊ Rub hands together covering all surfaces until dry quickly without wiping◊ Not recommended for infants ◊ Use in children under 6 years of age must be supervisedOther Information:
◊ Do not store above 105 F or 39 C
◊ May discolor some fabrics, wood finishes and plastics

Inactive Ingredients:

Water, Aloe Barbadensis Leaf Juice, Glycerin, Propylene Glycol, Carbomer, Aminomethyl Propanol, Hamamelis Virginiana (witchhazel) Leaf Extract, Fragrance